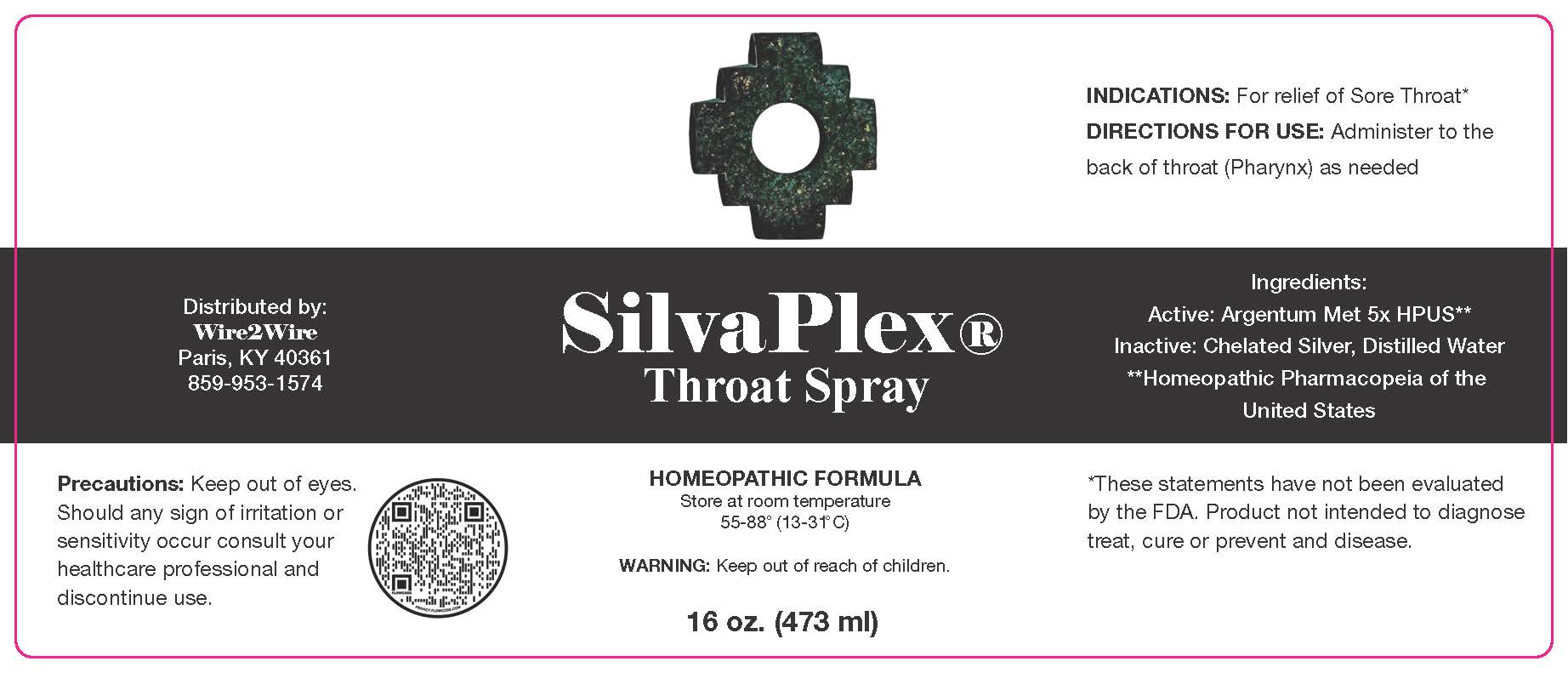 DRUG LABEL: SilvaPlex Throat
NDC: 72363-011 | Form: SPRAY
Manufacturer: AG Essence
Category: homeopathic | Type: HUMAN OTC DRUG LABEL
Date: 20251214

ACTIVE INGREDIENTS: SILVER 0.0006 g/473 g
INACTIVE INGREDIENTS: CITRIC ACID MONOHYDRATE 0.612 g/473 g; SILVER OXIDE 0.047 g/473 g; WATER 472.34 g/473 g

DIRECTIONS FOR USE:

Administer to the back of the throat (Pharynx) as needed.

WARNING:

Keep out of reach of children

Precautions:

Keep out of eyes.

Should any irritation or

sensitivity occur consult your

healthcare professional and

discontinue use.

Ingredients:

Active: Argentum Met 5X HPUS**

**Homeopathic Pharmacopeia of the United States

Ingredients:

Inactive: Chelated Silver, Distilled Water

INDICATIONS:

For relief of sore throat.*

*These statements have not been evaluated by the FDA.

Product not intended to diagnose, treat, cure or prevent desease.

Warning

Keep out of reach of children